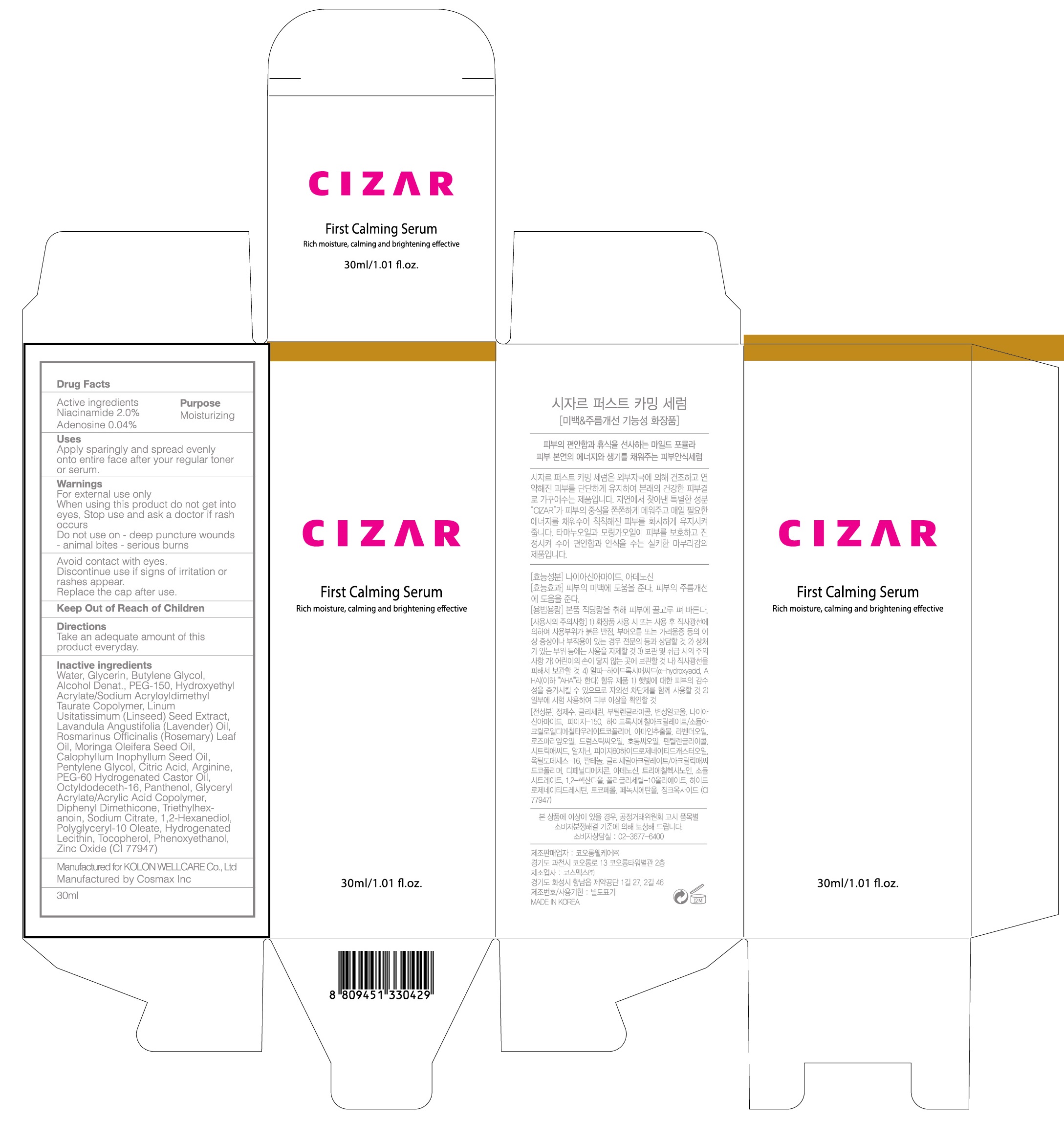 DRUG LABEL: CIZAR First Calming Serum
NDC: 71128-020 | Form: LIQUID
Manufacturer: Tissuegene,inc
Category: otc | Type: HUMAN OTC DRUG LABEL
Date: 20181217

ACTIVE INGREDIENTS: Niacinamide 0.6 g/30 mL; Adenosine 0.012 g/30 mL
INACTIVE INGREDIENTS: Water; Glycerin

ACTIVE INGREDIENT

Active ingredients: Niacinamide 2.0%, Adenosine 0.04%

INACTIVE INGREDIENT

Inactive ingredients: Water, Glycerin, Butylene Glycol, Alcohol Denat., PEG-150, Hydroxyethyl Acrylate/Sodium Acryloyldimethyl Taurate Copolymer, Linum Usitatissimum (Linseed) Seed Extract, Lavandula Angustifolia (Lavender) Oil, Rosmarinus Officinalis (Rosemary) Leaf Oil, Moringa Oleifera Seed Oil, Calophyllum Inophyllum Seed Oil, Pentylene Glycol, Citric Acid, Arginine, PEG-60 Hydrogenated Castor Oil, Octyldodeceth-16, Panthenol, Glyceryl Acrylate/Acrylic Acid Copolymer, Diphenyl Dimethicone, Triethylhexanoin, Sodium Citrate, 1,2-Hexanediol, Polyglyceryl-10 Oleate, Hydrogenated Lecithin, Tocopherol, Phenoxyethanol, Zinc Oxide (CI 77947)

PURPOSE

Purpose: Moisturizing

WARNINGS

For external use only When using this product do not get into eyes, Stop use and ask a doctor if rash occurs Do not use on - deep puncture wounds - animal bites - serious burns

Avoid contact with eyes. Discontinue use if signs of irritation or rashes appear. Replace the cap after use. Keep Out of Reach of Children

KEEP OUT OF REACH OF CHILDREN

Uses

Uses: Apply sparingly and spread evenly onto entire face after your regular toner or serum.

Directions

Directions: Take an adequate amount of this product everyday.